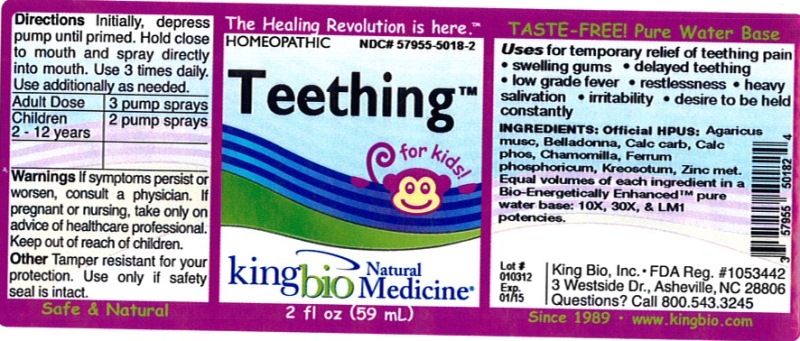 DRUG LABEL: Teething
NDC: 57955-5018 | Form: LIQUID
Manufacturer: King Bio Inc.
Category: homeopathic | Type: HUMAN OTC DRUG LABEL
Date: 20120614

ACTIVE INGREDIENTS: AMANITA MUSCARIA VAR. MUSCARIA FRUITING BODY 10 [hp_X]/59 mL; ATROPA BELLADONNA 10 [hp_X]/59 mL; OYSTER SHELL CALCIUM CARBONATE, CRUDE 10 [hp_X]/59 mL; TRIBASIC CALCIUM PHOSPHATE 10 [hp_X]/59 mL; MATRICARIA RECUTITA 10 [hp_X]/59 mL; FERROSOFERRIC PHOSPHATE 10 [hp_X]/59 mL; WOOD CREOSOTE 10 [hp_X]/59 mL; ZINC 10 [hp_X]/59 mL
INACTIVE INGREDIENTS: WATER

Teething

Active Ingredients

Official HPUS: Agaricus muscarius, Belladonna, Calcarea carbonica, Calcarea phosphorica, Chamomilla, Ferrum phosphoricum, Kreosotum and Zincum metallicum.

Reference image teething.jpg

Inactive Ingredient

Equal volumes of each ingredient in a Bio-Energetically Enhanced pure water base: 10X, 30X, and LM1 potencies.

Reference image teething.jpg

Purpose

Uses for temporary relief of teething pain

- swelling gums
- delayed teething
- low grade fever
- restlessness
- heavy salivation
- irritability
- desire to be held constantly

Reference image teething.jpg

Dosage and Administration

Directions: Initially, depress pump until primed. Hold close to mouth and spray directly into mouth. Use 3 times daily. Use additionally as needed.

Adult Dose 3 pump sprays

Children 2-12 years 2 pump sprays

Reference image teething.jpg

Warnings

If symptoms persist or worsen, consult a physician. If pregnant or nursing, take only on advice of a healthcare professional. Keep out of reach of children.

Other: Tamper resistant for your protection. Use only if safety seal is intact.

Reference image teething.jpg

Keep out of reach of children.

Reference image teething.jpg

Indications and Usage

Uses for temporary relief of teething pain: swelling gums, delayed teething, low grade fever, restlessness, heavy salivation, irritability, desire to be held constantly.

Reference image teething.jpg

PACKAGE LABEL

King Bio Inc.

3 Westside Drive

Asheville, NC 28806

Questions? Call 800.543.3245

www.kingbio.com

Safe and Natural

Reference image teething.jpg